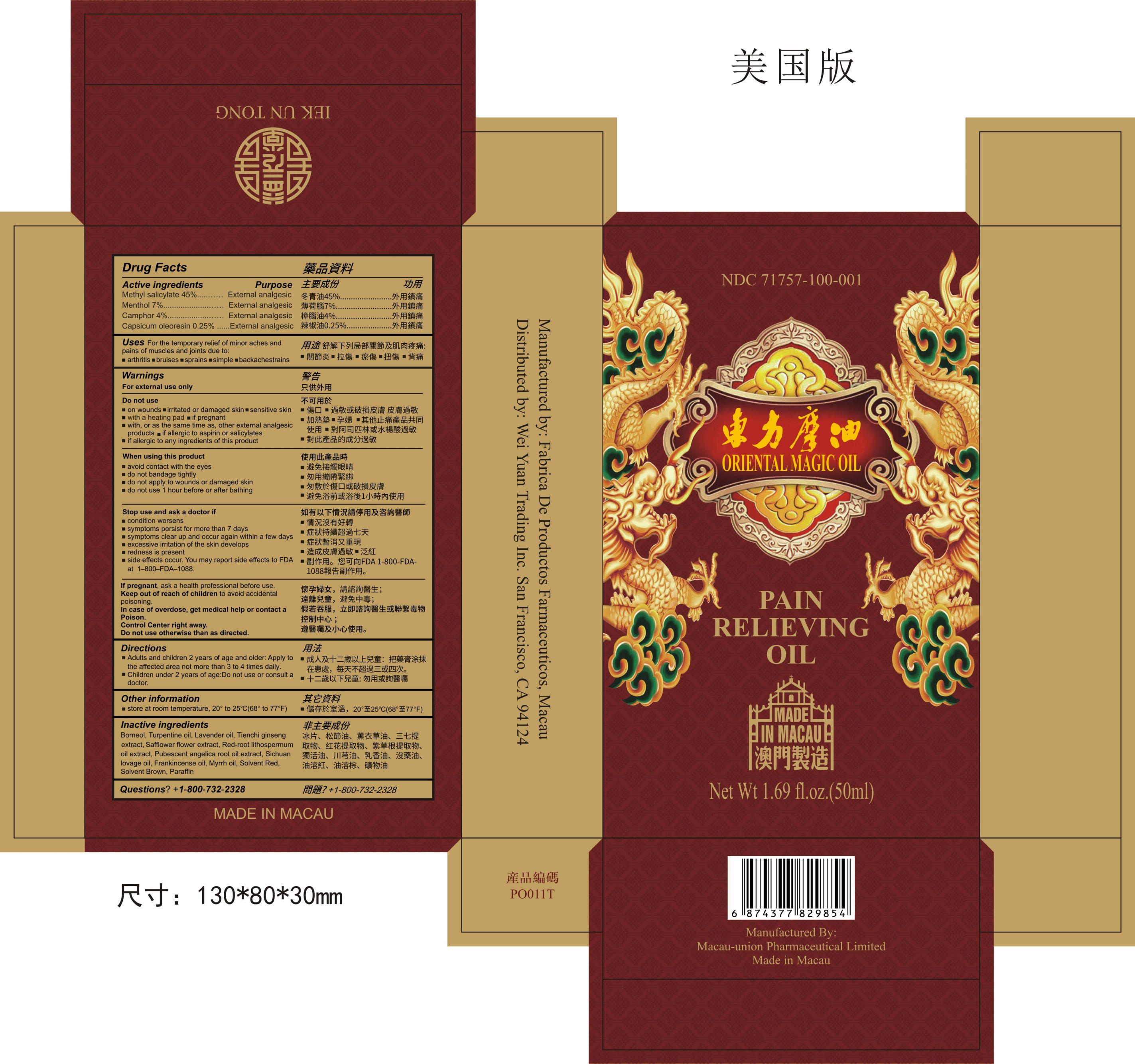 DRUG LABEL: Oriental Magic Oil
NDC: 71757-100 | Form: OIL
Manufacturer: Wei Yuan Trading Inc
Category: otc | Type: HUMAN OTC DRUG LABEL
Date: 20180405

ACTIVE INGREDIENTS: METHYL SALICYLATE 45 g/100 mL; MENTHOL 7 g/100 mL; CAMPHOR OIL 4 g/100 mL; CAPSICUM OLEORESIN 0.25 g/100 mL
INACTIVE INGREDIENTS: BORNEOL; TURPENTINE OIL; LAVENDER OIL; PANAX NOTOGINSENG ROOT; CARTHAMUS TINCTORIUS FLOWER OIL; LITHOSPERMUM OFFICINALE SEED OIL; ANGELICA PUBESCENS WHOLE; LIGUSTICUM SINENSE SUBSP. CHUANXIONG WHOLE; FRANKINCENSE OIL; MYRRH OIL; SOLVENT BROWN 1; SOLVENT RED 27; PARAFFIN

Oriental Magic Oil

Active ingredients

Methyl salicylate 45%......……….…….External analgesic
Menthol 7%.....................……….…….External analgesic
Camphor 4%...................……….…….External analgesic
Capsicum oleoresin 0.25%......…….External analgesic

Do not use otherwise than as directed

Keep out of reach of children to avoid accidental poisoning

If pregnant

If pregnant, ask a health professional before use

Directions

- Adults and children 2 years of age and older: Apply to the affected area not more than 3 to 4 times daily.
- Children under 2 years of age: Do not use or consult a doctor.

Other information

store at room temperature, 20° to 25°C(68° to 77F)

Inactive ingredients

Borneol, Turpentine oil, Lavender oil, Tienchi ginseng extract, Safflower flower extract, Red-root lithospermum oil extract, Pubescent angelica root oil extract, Sichuan lovage oil, Frankincense oil, Myrrh oil, Solvent Red, Solvent Brown, Paraffin

Questions?

+1-800-732-2328

For external use only

Purpose

External analgesic

Do not use

- on wounds
- irritated or damaged skin
- sensitive skin
- with a heating pad
- if pregnant
- with, or as the same time as, other external analgesic products
- if allergic to aspirin or salicylates
- if allergic to any ingredients of this product

When using this product

- avoid contact with the eyes
- do not bandage tightly
- do not apply to wounds or damaged skin
- do not use 1 hour before or after bathing

Stop use and ask a doctor if

- condition worsens
- symptoms persist for more than 7 days
- symptoms clear up and occur again within a few days
- excessive irritation of the skin develops
- redness is present
- side effects occur. You may report side effects to FDA at
  1–800–FDA–1088.

Warnings

For external use only

In case of overdose, get medical help or contact a Poison Control Center right away

Uses

For the temporary relief of minor pain and pains of muscles and joints due to:

- arthritis
- strains
- bruises
- sprains
- simple backache

Oriental Magic Oil Principal Display Panel

Oriental Magic Oil outer package